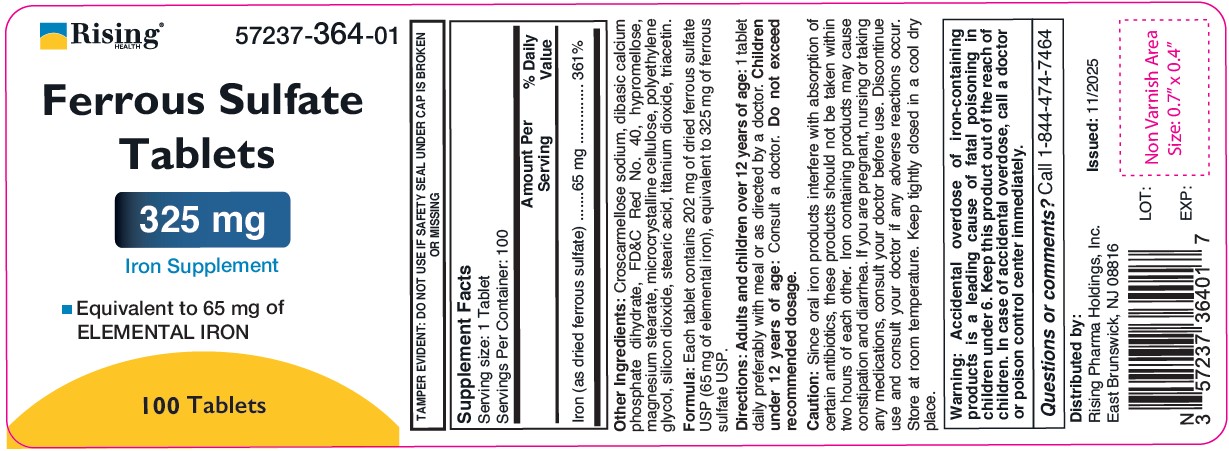 DRUG LABEL: Ferrous Sulfate
NDC: 57237-364 | Form: TABLET, FILM COATED
Manufacturer: Rising Pharma Holdings, Inc.
Category: other | Type: DIETARY SUPPLEMENT
Date: 20251113

ACTIVE INGREDIENTS: FERROUS SULFATE 65 mg/1 1
INACTIVE INGREDIENTS: CROSCARMELLOSE SODIUM; DIBASIC CALCIUM PHOSPHATE DIHYDRATE; FD&C RED NO. 40; HYPROMELLOSE, UNSPECIFIED; MAGNESIUM STEARATE; CELLULOSE, MICROCRYSTALLINE; POLYETHYLENE GLYCOL, UNSPECIFIED; SILICON DIOXIDE; STEARIC ACID; TITANIUM DIOXIDE; TRIACETIN

Ferrous Sulfate Tablets
325 mg
Iron Supplement

Supplement Facts

Serving size: 1 Tablet

Servings Per Container: 100 and 1,000

 | Amount Per Serving | % Daily Value
Iron (as dried ferrous sulfate) | 65 mg | 361%

Other Ingredients: Croscarmellose sodium, dibasic calcium phosphate dihydrate, FD&C Red No. 40, hypromellose, magnesium stearate, microcrystalline cellulose, polyethylene glycol, silicon dioxide, stearic acid, titanium dioxide, triacetin.

Formula: Each tablet contains 202 mg of dried ferrous sulfate USP (65 mg of elemental iron), equivalent to 325 mg of ferrous sulfate USP.

Directions:

Adults and children over 12 years of age: 1 tablet daily preferably with a meal or as directed by a doctor. Children under 12 years of age: Consult a doctor. Do not exceed recommended dosage.

Caution:

Since oral iron products interfere with absorption of certain antibiotics, these products should not be taken within two hours of each other. Iron containing products may cause constipation and diarrhea. If you are pregnant, nursing or taking any medications, consult your doctor before use. Discontinue use and consult your doctor if any adverse reactions occur.

Store at room temperature. Keep tightly closed in a cool dry place.

Warning: Accidental overdose of iron-containing products is a leading cause of fatal poisoning in children under 6. Keep this product out of the reach of children. In case of accidental overdose, call a doctor or Poison Control Center immediately.

Questions or comments? call 1-844-474-7464

Distributed by:

Rising Pharma Holdings, Inc.

East Brunswick, NJ 08816